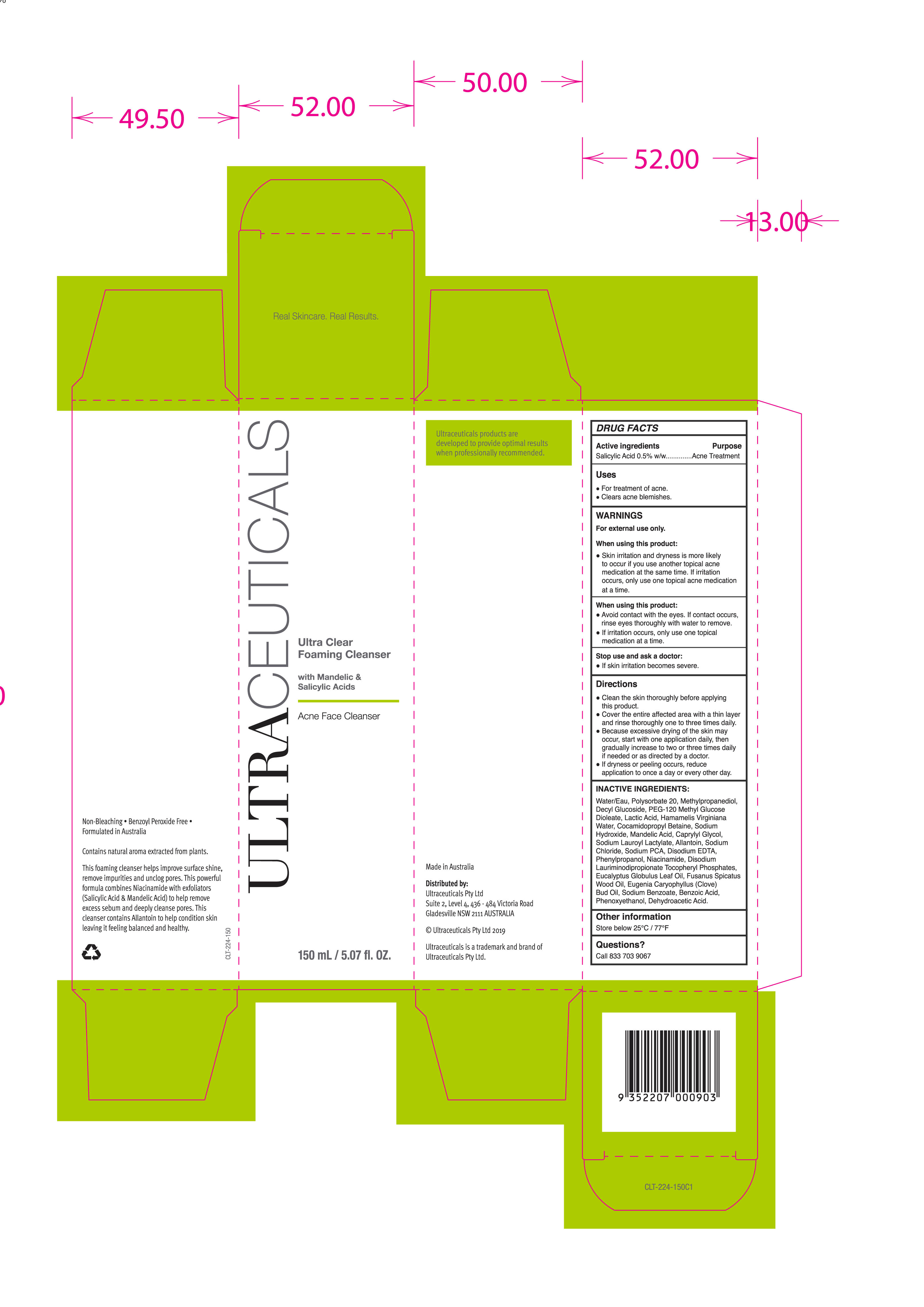 DRUG LABEL: Ultra Clear Foaming Cleanser
NDC: 10028-050 | Form: LOTION
Manufacturer: ULTRACEUTICALS PTY LIMITED
Category: otc | Type: HUMAN OTC DRUG LABEL
Date: 20251007

ACTIVE INGREDIENTS: SALICYLIC ACID 0.5 g/100 mL
INACTIVE INGREDIENTS: PHENYLPROPANOL; NIACINAMIDE; SANTALUM SPICATUM OIL; PEG-120 METHYL GLUCOSE DIOLEATE; LACTIC ACID; HAMAMELIS VIRGINIANA TOP WATER; CLOVE OIL; COCAMIDOPROPYL BETAINE; SODIUM PYRROLIDONE CARBOXYLATE; ALLANTOIN; POLYSORBATE 20; EUCALYPTUS GLOBULUS LEAF; SODIUM BENZOATE; MANDELIC ACID; SODIUM LAUROYL LACTYLATE; METHYLPROPANEDIOL; DECYL GLUCOSIDE; PHENOXYETHANOL; DEHYDROACETIC ACID; BENZOIC ACID; SODIUM HYDROXIDE; EDETATE DISODIUM; CAPRYLYL GLYCOL; DISODIUM LAURIMINODIPROPIONATE TOCOPHERYL PHOSPHATES; SODIUM CHLORIDE; WATER

Ultra Clear Foaming Cleanser
Acne Face Cleanser

Active Ingredients Purpose

Salicylic Acid 0.5% w/w Acne Treatment

Uses

For treatment of Acne

Clear acne blemishes

When using this product:

Avoid contact with eyes. If contact occurs, rinse eyes thoroughly with water to remove.

If irritation occurs, only use one topical medication

Stop use and ask a doctor:

if skin irritation becomes severe

Warnings

For External use only.

- Skin irritation and dryness is more likely to occur if you use another topical acne medication at the same time. If irritation occurs, only use one topical acne medication at a time.

Directions

Clean the skin thoroughly before applying this product.

Cover the entire affected area with a thin layer and rinse thoroughly one to three times daily.

Because excessive drying of the skin may occur, start with one application daily, then gradually increase to two or three times daily if needed or as directed by a doctor

If dryness or peeling occurs, reduce application to once a day or every other day.

Inactive Ingredients

Water/Eau, Polysorbate 20, Methylpropanediol, Decyl Glucoside, PEG-120 Methyl Glucose Dioleate, Lactic Acid, Hamamelis Virginiana Water, Cocamidopropyl Betaine, Sodium Hydroxide, Mandelic Acid, Caprylyl Glycol, Sodium Lauroyl Lactylate, Allantoin, Sodium Chloride, Sodium PCA, Disodium EDTA, Phenylpropanol, Niacinamide, Disodium Lauriminodipropionate Tocopheryl Phosphates, Eucalyptus Globulus Leaf Oil, Fusanus Spicatus Wood Oil, Eugenia Caryophyllus (Clove) Bud Oil, Sodium Benzoate, Benzoic acid, Phenoxyethanol, Dehydroacetic Acid.

PACKAGE LABEL

Ultraceuticals

Ultra Clear Foaming Cleanser

with Mandelic & Salicylic Acid

Acne Face Cleanser

150mL / 5.07 fl. Oz.